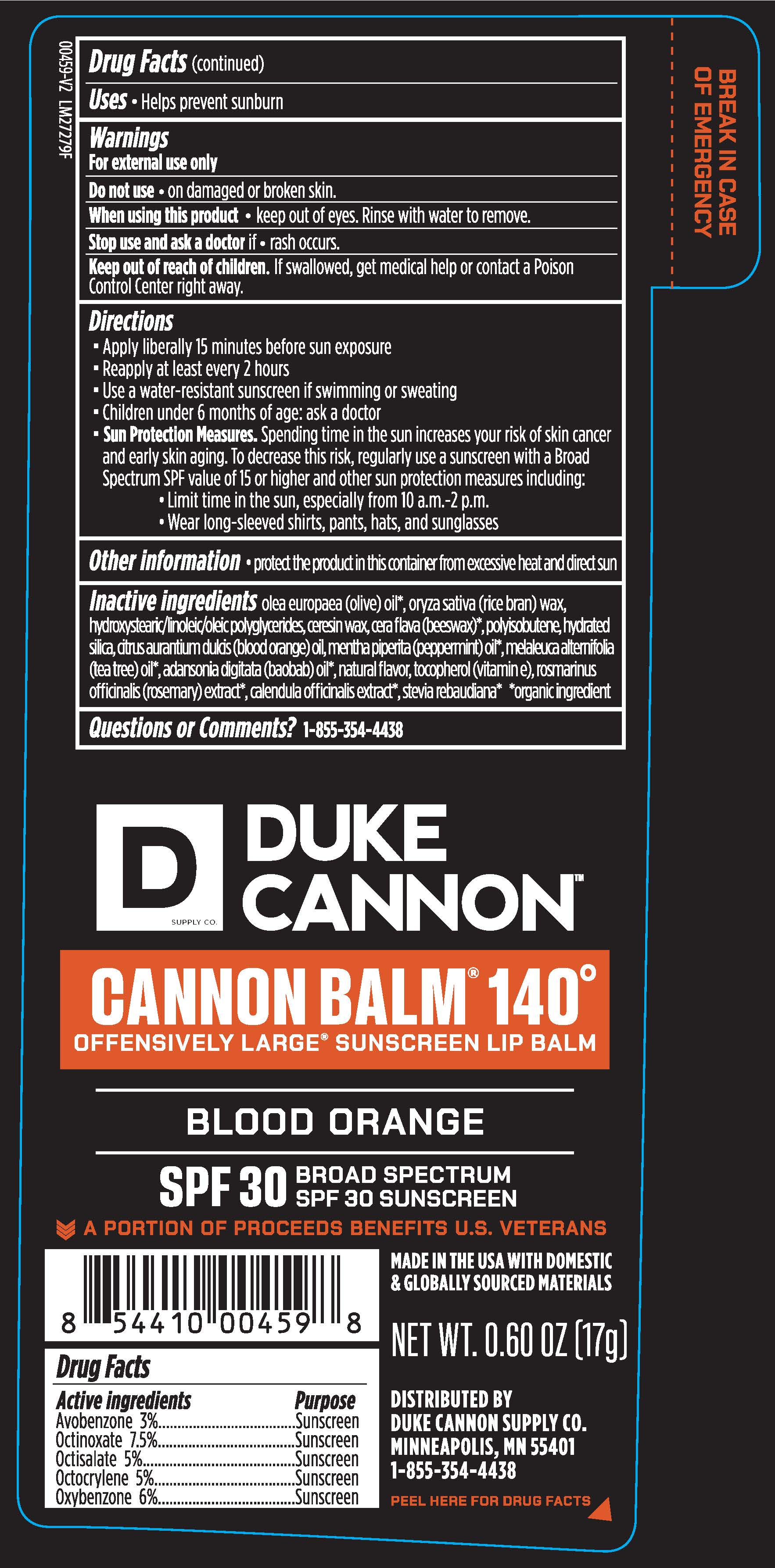 DRUG LABEL: CANNON BALM 140
NDC: 71782-141 | Form: STICK
Manufacturer: DUKE CANNON SUPPLY CO.
Category: otc | Type: HUMAN OTC DRUG LABEL
Date: 20251203

ACTIVE INGREDIENTS: OCTINOXATE 1.28 g/17 g; AVOBENZONE 0.51 g/17 g; OCTISALATE 0.85 g/17 g; OXYBENZONE 1.02 g/17 g; OCTOCRYLENE 0.85 g/17 g
INACTIVE INGREDIENTS: ADANSONIA DIGITATA SEED OIL; YELLOW WAX; ORANGE OIL; CALENDULA OFFICINALIS FLOWER; CASTOR OIL; CERESIN; HYDRATED SILICA; 12-HYDROXYSTEARIC ACID; LINOLEIC ACID; OLEIC ACID; OLIVE OIL; PEPPERMINT OIL; POLYISOBUTYLENE (1000 MW); RICE BRAN; ROSEMARY OIL; STEVIA LEAF; TEA TREE OIL; .ALPHA.-TOCOPHEROL ACETATE

90341 Duke Cannon SPF 30 Cannonbalm 140

Active Ingredients

Avobenzone 3%

Octinoxate 7.5%

Octisalate 5%

Octocrylene 5%

Oxybenzone 6%

Purpose

Sunscreen

Sunscreen

Sunscreen

Sunscreen

Sunscreen

INDICATIONS AND USAGE

Uses • helps prevent sunburn

Warnings

For external use only

Do not use • on damaged or broken skin

When using this product • keep out of eyes. Rinse with water to remove.

Stop use and ask doctor if • rash occurs

Keep out of reach of children. If swallowed, get medical help or contact a Poison Control Center right away.

Directions

- apply liberally 15 minutes before sun exposure
- reapply at least every 2 hours
- use a water-resistant sunscreen if swimming or sweating
- children under 6 months of age: ask a doctor
- Sun Protection Measures. Spending time in the sun increases your risk of skin cancer and early skin aging. To decrease this risk, regularly use a sunscreen with a broad spectrum value of 15 or higher and other sun protection measures including:
- limit time in the sun, especially from 10 a.m.-2 p.m.
- wear long-sleeved shirts, pants, hats and sunglasses

Other Information • protect the product in this container from excessive heat and direct sun.

INACTIVE INGREDIENT

Inactive Ingredients olea europaea (olive) oil*, oryza sativa (rice bran) wax, hydroxystearic/linoleic/oleic polyglycerides, ceresin wax, cera flava (beeswax)*, polyisobutene, hydrated silica, citrus aurantium dulcis (blood orange) oil, mentha piperita (peppermint) oil*, melaleuca alternifolia (tea tree) oil*, adansonia digitata (baobab) oil*, natural flavor, tocopherol (vitamin e), rosmarinus officinalis (rosemary) extract*, calendula officinalis extract*, stevia rebaudiana* *organic ingredient

Questions or Comments? 1-855-354-4438

DUKE

CANNON

SUPPLY CO.

CANNON BALM® 140°

OFFENSIVELY LARGE® SUNSCREEN LIP BALM

BLOOD ORANGE

SPF 30 BROAD SPECTRUM SPF 30 SUNSCREEN

A PORTION OF PROCEEDS BENEFITS U.S. VETERANS

MADE IN USA WITH DOMESTIC

& GLOBALLY SOURCED MATERIALS

NET WT. 0.60 OZ (17g)

DISTRIBUTED BY

DUKE CANNON SUPPLY CO.

MINNEAPOLIS, MN 55401

PEEL HERE FOR DRUG FACTS

BREAK IN CASE OF EMERGENCY

RECENT MAJOR CHANGES

Uses section updates: Added a bullet point

Directions section updates: Moved "Children under 6" bullet point so it is before "Sun Protection Measures." Added a bullet before "sun protection measures"